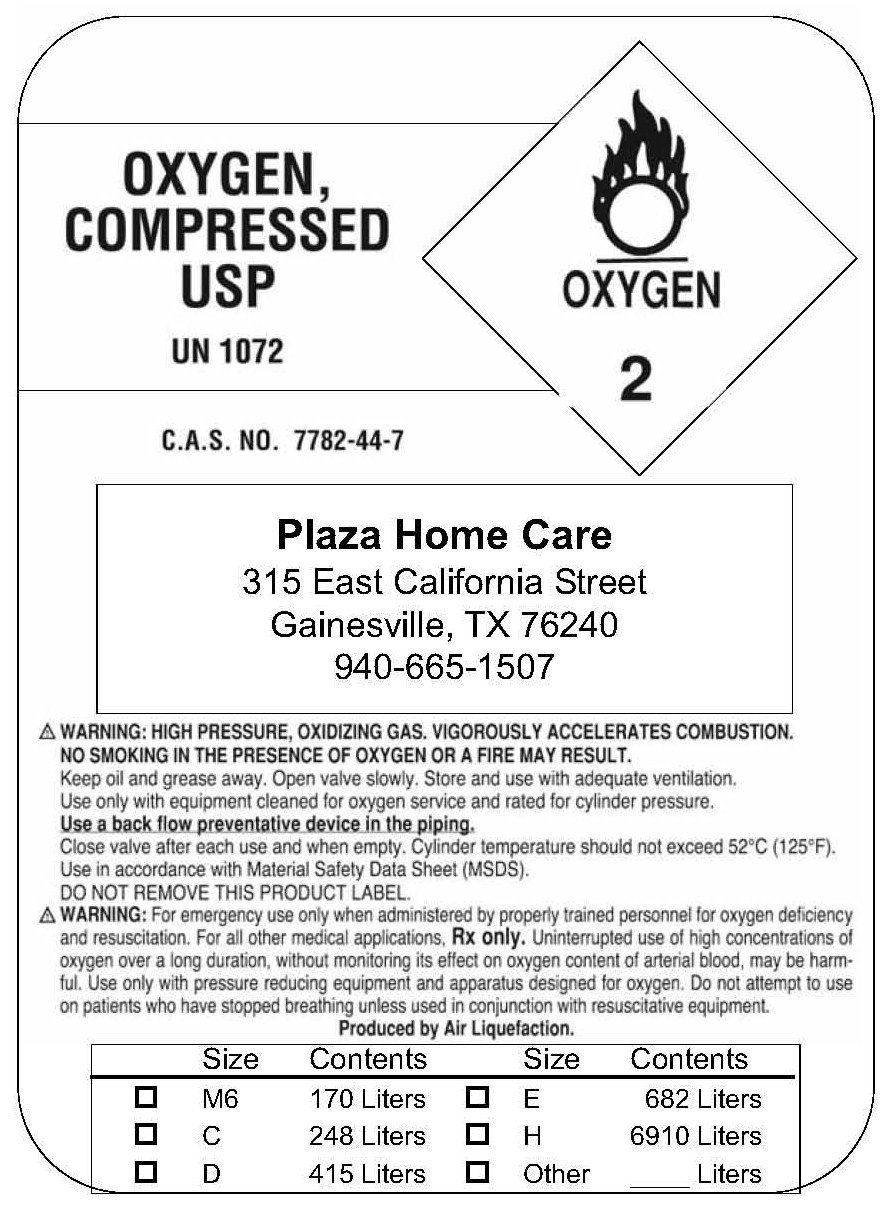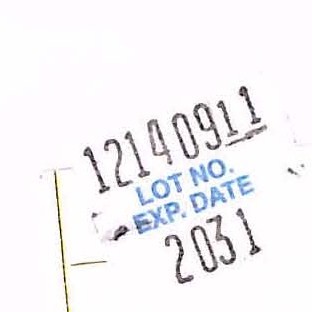 DRUG LABEL: Oxygen
NDC: 67441-0001 | Form: GAS
Manufacturer: Plaza Home Care, Inc. 
Category: prescription | Type: HUMAN PRESCRIPTION DRUG LABEL
Date: 20091230

ACTIVE INGREDIENTS: Oxygen 99 L/100 L

Oxygen